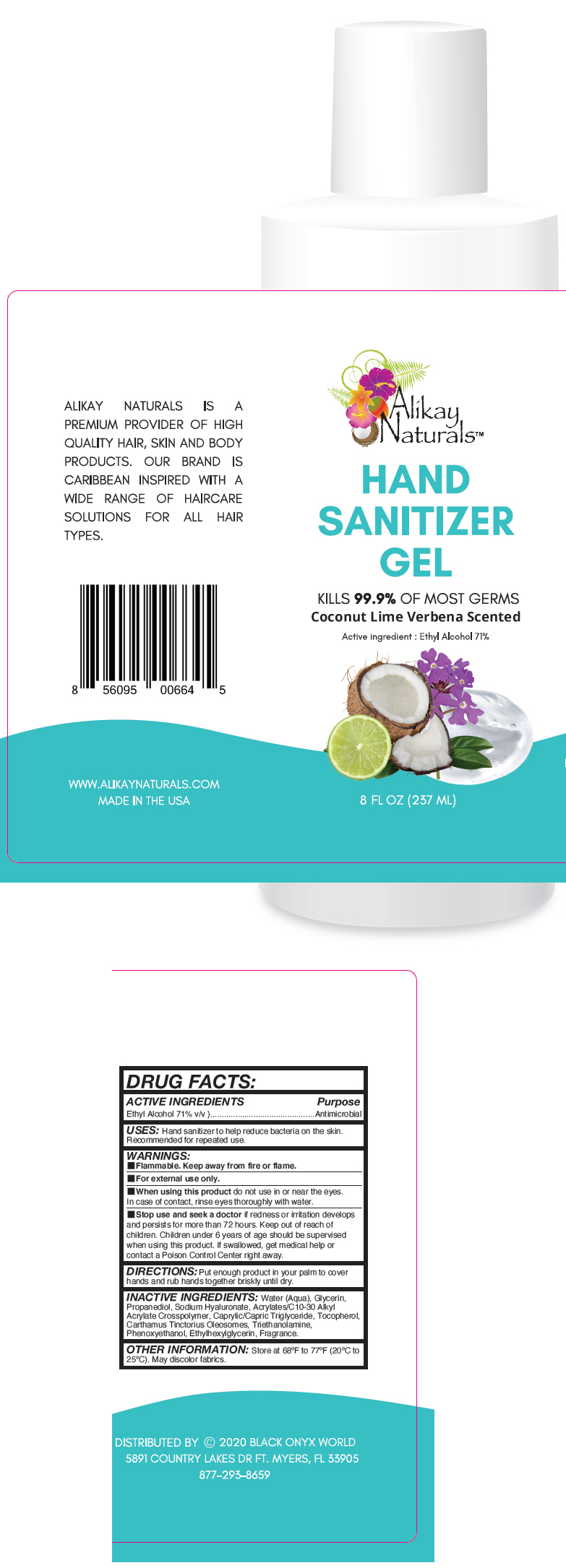 DRUG LABEL: Alikay Naturals - Hand Sanitizer
NDC: 66163-1504 | Form: GEL
Manufacturer: Cosmetic Solutions LLC
Category: otc | Type: HUMAN OTC DRUG LABEL
Date: 20200601

ACTIVE INGREDIENTS: Alcohol 71 mL/100 mL
INACTIVE INGREDIENTS: Water; Glycerin; Propanediol; Hyaluronate Sodium; Carbomer Interpolymer Type A (Allyl Sucrose Crosslinked); Medium-Chain Triglycerides; Tocopherol; Carthamus Tinctorius Seed Oleosomes; Trolamine; Phenoxyethanol; Ethylhexylglycerin

Alikay Naturals™ - Hand Sanitizer Gel

DRUG FACTS:

ACTIVE INGREDIENTS

Ethyl Alcohol 71% v/v

Purpose

Antimicrobial

USES

Hand sanitizer to help reduce bacteria on the skin. Recommended for repeated use.

WARNINGS

- Flammable. Keep away from fire or flame.
- For external use only.

- When using this product do not use in or near the eyes. In case of contact, rinse eyes thoroughly with water.

- Stop use and seek a doctor if redness or irritation develops and persists for more than 72 hours.

Keep out of reach of children. Children under 6 years of age should be supervised when using this product. If swallowed, get medical help or contact a Poison Control Center right away.

DIRECTIONS

Put enough product in your palm to cover hands and rub hands together briskly until dry.

INACTIVE INGREDIENTS

Water (Aqua), Glycerin, Propanediol, Sodium Hyaluronate, Acrylates/C10-30 Alkyl Acrylate Crosspolymer, Caprylic/Capric Triglyceride, Tocopherol, Carthamus Tinctorius Oleosomes, Triethanolamine, Phenoxyethanol, Ethylhexylglycerin, Fragrance.

OTHER INFORMATION

Store at 68°F to 77°F (20°C to 25°C). May discolor fabrics.

DISTRIBUTED BY © 2020 BLACK ONYX WORLD
5891 COUNTRY LAKES DR FT. MYERS, FL 33905

PRINCIPAL DISPLAY PANEL - 237 ML Bottle Label

Alikay
Naturals™

HAND
SANITIZER
GEL

KILLS 99.9% OF MOST GERMS

Coconut Lime Verbena Scented

Active ingredient : Ethyl Alcohol 71%

8 FL OZ (237 ML)